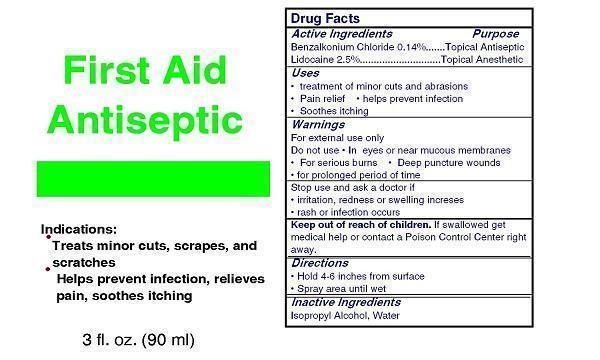 DRUG LABEL: Your Logo Here Antiseptic First Aid
NDC: 52982-120 | Form: SPRAY, METERED
Manufacturer: Dixon Investments, Inc.
Category: otc | Type: HUMAN OTC DRUG LABEL
Date: 20130531

ACTIVE INGREDIENTS: LIDOCAINE 1912.5 mg/90 mL; BENZALKONIUM CHLORIDE 107.1 mg/90 mL
INACTIVE INGREDIENTS: ISOPROPYL ALCOHOL; WATER

Your Logo Here Antiseptic Pump Spray

Active Ingredients

Benzalkonium Chloride 0.14%
Lidocaine 2.5%

Purposes

Topical Antiseptic
Topical Anesthetic

Uses

Treatment of minor cuts and abrasions
Pain Relief
Helps prevent infection
Soothes itching

Warnings

For external use only

Do not use

In eyes or near mucous membranes
For serious burns
Deep puncture wounds
For prolonged period of time

Stop use and ask a doctor if

Irritation, redness, or swelling increases
Rash or infection occurs

Directions

Hold 4-6 inches from surface
Spray area until wet

Inactive Ingredients

Isopropyl Alcohol
Water